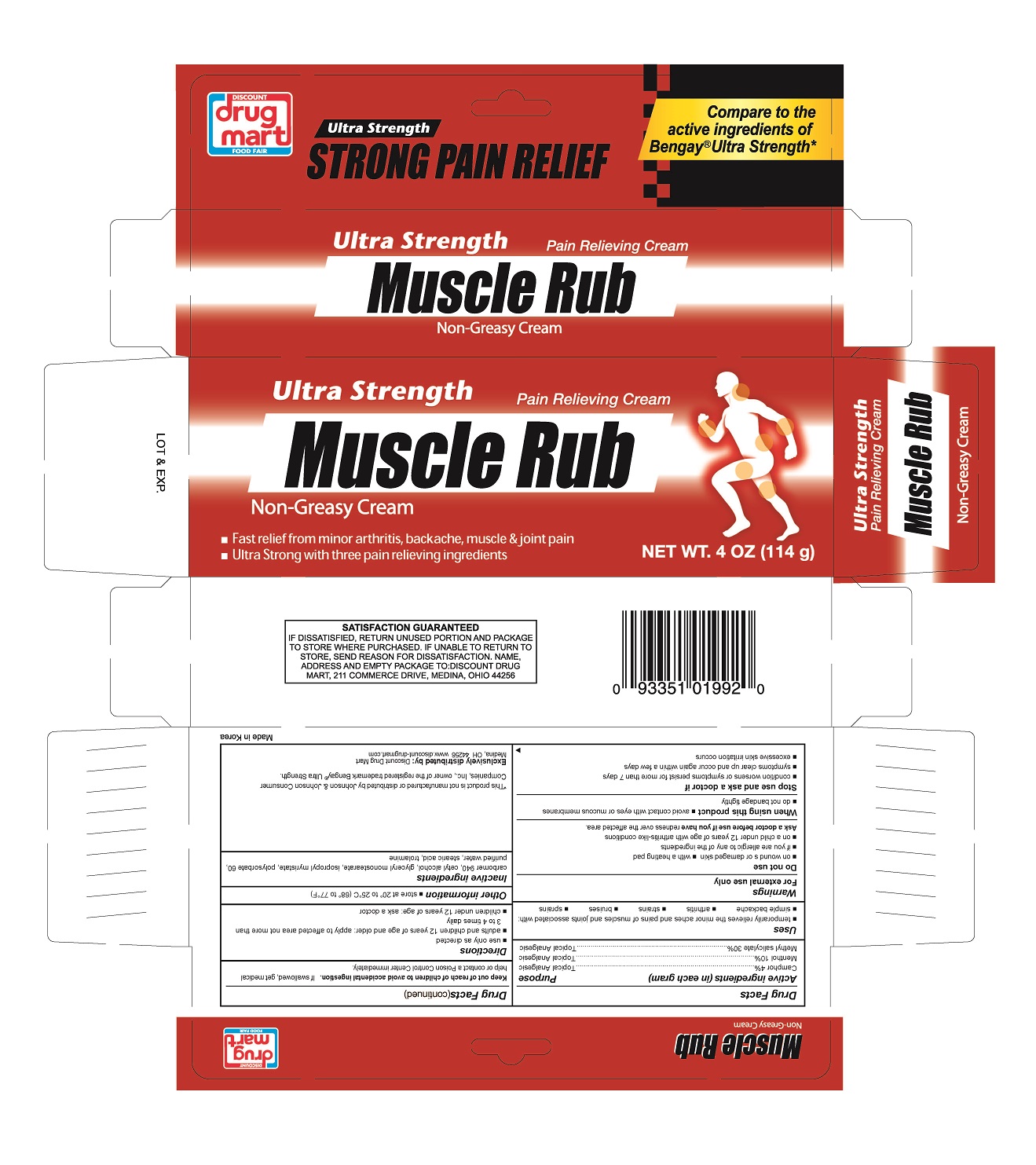 DRUG LABEL: Pain Relief Rub
NDC: 53943-992 | Form: CREAM
Manufacturer: Discount Drug Mart, Inc.
Category: otc | Type: HUMAN OTC DRUG LABEL
Date: 20171227

ACTIVE INGREDIENTS: MENTHOL 10 g/100 g; MENTHYL SALICYLATE, (+/-)- 30 g/100 g; CAMPHOR (NATURAL) 4 g/100 g
INACTIVE INGREDIENTS: CARBOMER 940; CETYL ALCOHOL; GLYCERYL MONOSTEARATE; ISOPROPYL MYRISTATE; POLYSORBATE 60; WATER; STEARIC ACID; TROLAMINE

Drug Facts

Active Ingredients

Camphor 4%

Menthol 10$

Methyl salicylate 30%

PURPOSE

Topical analgesic

Topical analgesic

Topical analgesic

Uses

temporarily relieves the minor aches and pains of muscle and joints associated with: simple backache, arthritis, bruises, sprains

WARNINGS

For external use only.

Do not use

- on wounds or damaged skin
- with a heating pad
- if you are allergic to any of the ingredients
- on a child under 12 years of age with arthritis-like conditions

Ask a doctor before use if you have

redness over the affected area

When using this product

- avoid contact with eyes or mucous membranes
- do not bandage tightly

Stop use and ask a doctor if

- condition worsens or symptoms persist for more than 7 days
- symptoms clear up and occur again within a few days
- excessive skin irritation occurs

Keep out of reach of children to avoid accidental ingestion.

If swallowed, get medical help or contact a Poison Control Center immediately

Directions

- use only as directed
- adults and children 12 years of age and older: apply to affected area not more than 3 to 4 times daily
- children under 12 years of age: ak a doctor

Other information

- Store at 20° to 25°C (68°to 77° F)

Inactive Ingredients

carbomer940, cetyl alcohol, glyceryl monostearate, isopropyl myristate, polysorbate60, purified water, stearic acid, trolamine

PACKAGE LABEL

Pain Relief Rub